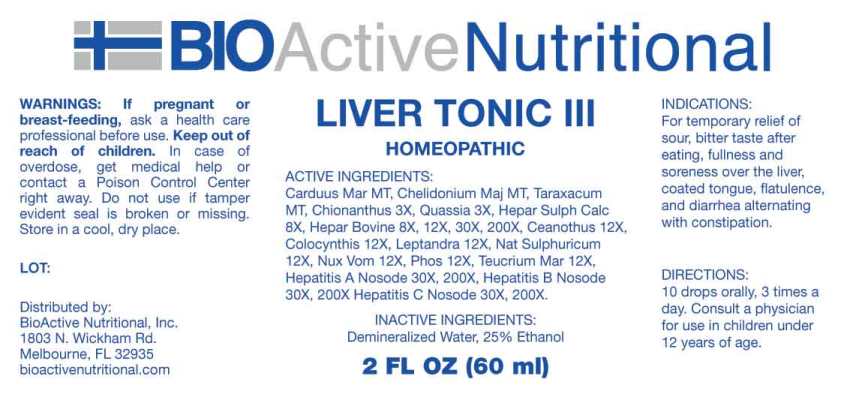 DRUG LABEL: Liver Tonic
NDC: 43857-0107 | Form: LIQUID
Manufacturer: BioActive Nutritional, Inc.
Category: homeopathic | Type: HUMAN OTC DRUG LABEL
Date: 20240419

ACTIVE INGREDIENTS: MILK THISTLE 1 [hp_X]/1 mL; CHELIDONIUM MAJUS WHOLE 1 [hp_X]/1 mL; TARAXACUM OFFICINALE 1 [hp_X]/1 mL; CHIONANTHUS VIRGINICUS BARK 3 [hp_X]/1 mL; QUASSIA AMARA WOOD 3 [hp_X]/1 mL; CALCIUM SULFIDE 8 [hp_X]/1 mL; BEEF LIVER 8 [hp_X]/1 mL; CEANOTHUS AMERICANUS LEAF 12 [hp_X]/1 mL; CITRULLUS COLOCYNTHIS FRUIT PULP 12 [hp_X]/1 mL; VERONICASTRUM VIRGINICUM ROOT 12 [hp_X]/1 mL; SODIUM SULFATE 12 [hp_X]/1 mL; STRYCHNOS NUX-VOMICA SEED 12 [hp_X]/1 mL; PHOSPHORUS 12 [hp_X]/1 mL; TEUCRIUM MARUM WHOLE 12 [hp_X]/1 mL; HEPATITIS A VIRUS 30 [hp_X]/1 mL; HEPATITIS B VIRUS 30 [hp_X]/1 mL; HEPATITIS C VIRUS 30 [hp_X]/1 mL
INACTIVE INGREDIENTS: WATER; ALCOHOL

DRUG FACTS:

ACTIVE INGREDIENTS:

Carduus Marianus 1X, Chelidonium Majus 1X, Taraxacum Officinale 1X, Chionanthus Virginica 3X, Quassia Amara 3X, Hepar Sulphuris Calcareum 8X, Hepar Bovinum 8X, 12X, 30X, 200X, Ceanothus Americanus 12X, Colocynthis 12X, Leptandra Virginica 12X, Natrum Sulphuricum 12X, Nux Vomica 12X, Phosphorus 12X, Teucrium Marum 12X, Hepatitis A 30X, 200X, Hepatitis B 30X, 200X, Hepatitis C 30X, 200X.

INDICATIONS:

For temporary relief of sour, bitter taste after eating, fullness and soreness over the liver, coated tongue, flatulence, and diarrhea alternating with constipation.

WARNINGS:

If pregnant or breast-feeding, ask a health care professional before use.

Keep out of reach of children. In case of overdose, get medical help or contact a Poison Control Center right away.

Do not use if tamper evident seal is broken or missing.

Store in cool, dry place.

DIRECTIONS:

10 drops orally, 3 times a day. Consult a physician for use in children under 12 years of age.

INACTIVE INGREDIENTS:

Demineralized Water, 25% Ethanol.

KEEP OUT OF REACH OF CHILDREN:

In case of overdose, get medical help or contact a Poison Control Center right away.

INDICATIONS:

For temporary relief of sour, bitter taste after eating, fullness and soreness over the liver, coated tongue, flatulence, and diarrhea alternating with constipation.

QUESTIONS:

Distributed by:

BioActive Nutritional, Inc.

1803 N. Wickham Rd.

Melbourne, FL 32935

bioactivenutritional.com

PACKAGE LABEL DISPLAY:

BioActive Homeopathic

LIVER TONIC III

HOMEOPATHIC

2 FL OZ (60 ml)